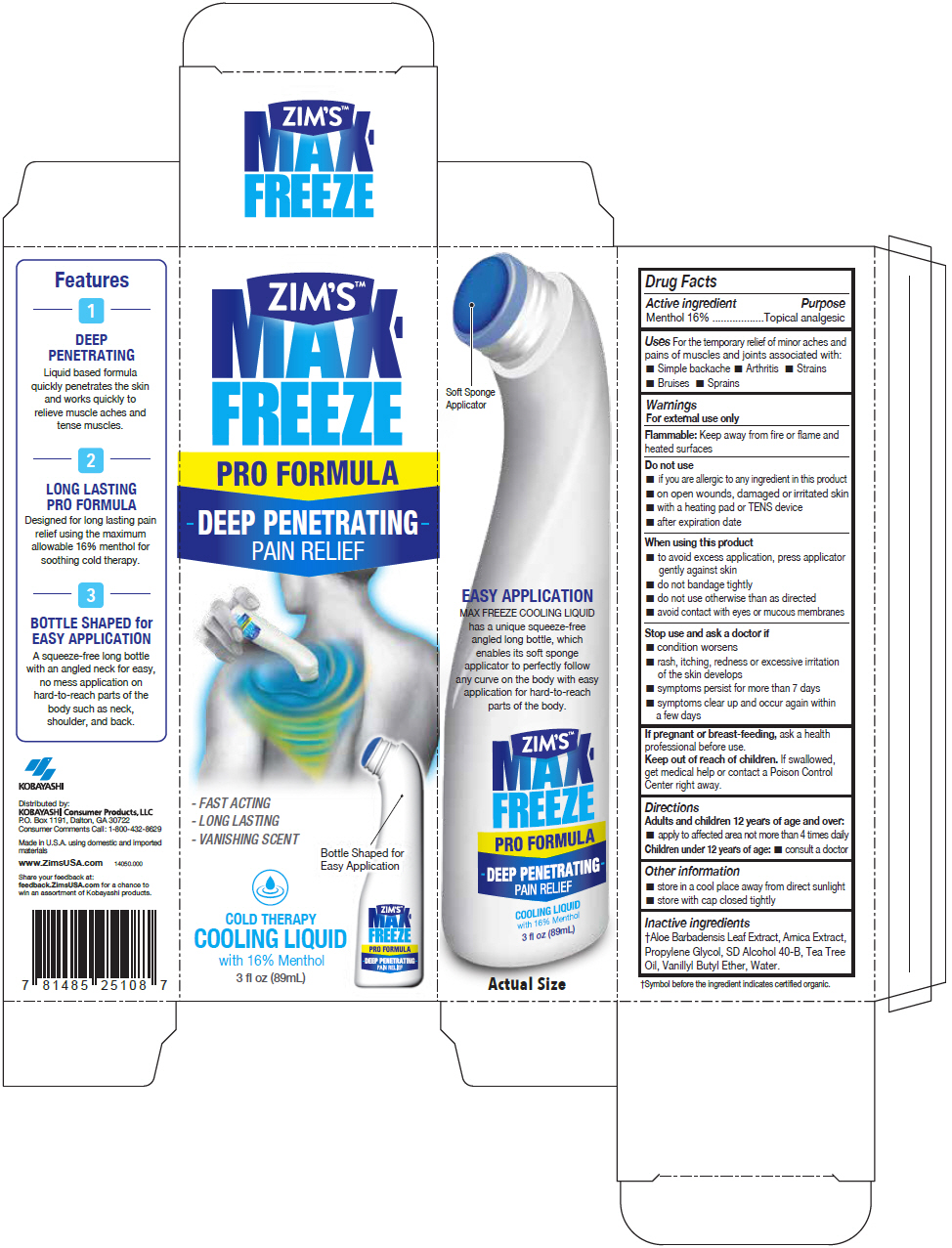 DRUG LABEL: ZIMS MAX FREEZE 
NDC: 54273-009 | Form: LIQUID
Manufacturer: KOBAYASHI Healthcare International, Inc.
Category: otc | Type: HUMAN OTC DRUG LABEL
Date: 20231116

ACTIVE INGREDIENTS: MENTHOL, UNSPECIFIED FORM 160 mg/1 mL
INACTIVE INGREDIENTS: ALOE VERA LEAF; ARNICA MONTANA WHOLE; VANILLYL BUTYL ETHER; TEA TREE OIL; ALCOHOL; WATER; PROPYLENE GLYCOL

ZIM'S™ MAX FREEZE
PRO FORMULA

Drug Facts

Active ingredient

Menthol 16%

Purpose

Topical analgesic

Uses

For the temporary relief of minor aches and pains of muscles and joints associated with:

- Simple backache
- Arthritis
- Strains
- Bruises
- Sprains

Warnings

For external use only

Flammable

Keep away from fire or flame and heated surfaces

Do not use

- if you are allergic to any ingredient in this product
- on open wounds, damaged or irritated skin
- with a heating pad or TENS device
- after expiration date

When using this product

- to avoid excess application, press applicator gently against skin
- do not bandage tightly
- do not use otherwise than as directed
- avoid contact with eyes or mucous membranes

Stop use and ask a doctor if

- condition worsens
- rash, itching, redness or excessive irritation of the skin develops
- symptoms persist for more than 7 days
- symptoms clear up and occur again within a few days

PREGNANCY OR BREAST FEEDING

If pregnant or breast-feeding, ask a health professional before use.

Keep out of reach of children. If swallowed, get medical help or contact a Poison Control Center right away.

Directions

Adults and children 12 years of age and over:

- apply to affected area not more than 4 times daily

Children under 12 years of age:

- consult a doctor

Other information

- store in a cool place away from direct sunlight
- store with cap closed tightly

Inactive ingredients

†Aloe Barbadensis Leaf Extract, Arnica Extract, Propylene Glycol, SD Alcohol 40-B, Tea Tree Oil, Vanillyl Butyl Ether, Water.

†Symbol before the ingredient indicates certified organic.

QUESTIONS

Consumer Comments Call: 1-800-432-8629

Distributed by:
KOBAYASHI Consumer Products, LLC
P.O. Box 1191, Dalton, GA 30722

PRINCIPAL DISPLAY PANEL - 89 mL Bottle Carton

ZIM'S™
MAX-
FREEZE
PRO FORMULA

DEEP PENETRATING
PAIN RELIEF

- FAST ACTING
- LONG LASTING
- VANISHING SCENT

Bottle Shaped for
Easy Application

COLD THERAPY
COOLING LIQUID
with 16% Menthol

3 fl oz (89mL)